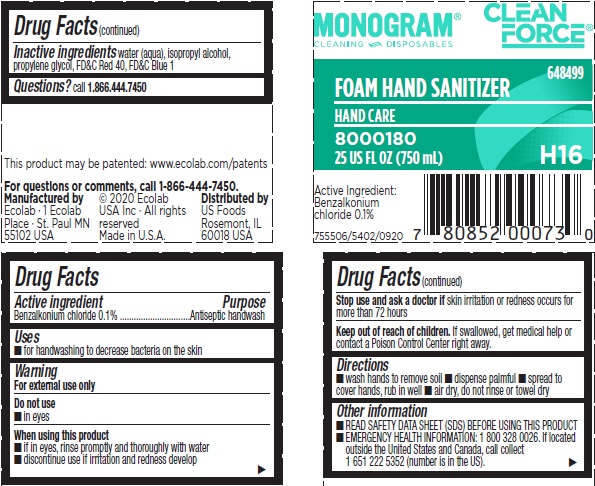 DRUG LABEL: Clean Force
NDC: 47593-586 | Form: LIQUID
Manufacturer: Ecolab Inc.
Category: otc | Type: HUMAN OTC DRUG LABEL
Date: 20251230

ACTIVE INGREDIENTS: BENZALKONIUM CHLORIDE 1 mg/1 mL
INACTIVE INGREDIENTS: WATER; ISOPROPYL ALCOHOL; PROPYLENE GLYCOL; FD&C RED NO. 40; FD&C BLUE NO. 1

Drug Facts

Active Ingredient

Benzalkonium chloride 0.1%

Purpose

Antiseptic handwash

Uses

- for handwashing to decrease bacteria on the skin

Warnings

For external use only

Do not use

- In eyes

When using this product

- If in eyes, rinse promptly and thoroughly with water
- discontinue use if irritation and redness develop

Stop use and ask a doctor if skin irritation or redness occurs for more than 72 hours

Keep out of reach of children. If swallowed, get medical help or contact a Poison Control Center right away.

Directions

- wash hands to remove soil
- dispense palmful
- spread to cover hands, rub in well
- air dry, do not rinse or towel dry

Other information

- READ SAFETY DATA SHEET (SDS) BEFORE USING THIS PRODUCT
- EMERGENCY HEALTH INFORMATION: 1 800 328 0026. If located outside the United States and Canada, call collect 1 651 222 5352 (number is in the US).

INACTIVE INGREDIENT

Inactive ingredients water (aqua), isopropyl alcohol, propylene glycol, FD&C red 40, FD&C blue 1

Questions? call 1.866.444.7450

Principal display panel and representative label

MONOGRAM CLEAN FORCE

CLEANING DISPOSABLES

FOAM HAND SANITIZER

Hand Care

8000180

25 US FL OZ (750 mL) H16

Active ingredient

Benzalkonium

chloride 0.1%

755506/5402/0920

This product may be patented: www.ecolab.com/patents

For questions or comments,

call 1-866-444-7450

Manufactured by | (c) 2020 Ecolab | Distributed by
Ecolab - 1 Ecolab | USA Inc. - All rights | US Foods
Place - St. Paul MN | reserved | Rosemont, IL
55102 USA | Made in USA | 60018 USA